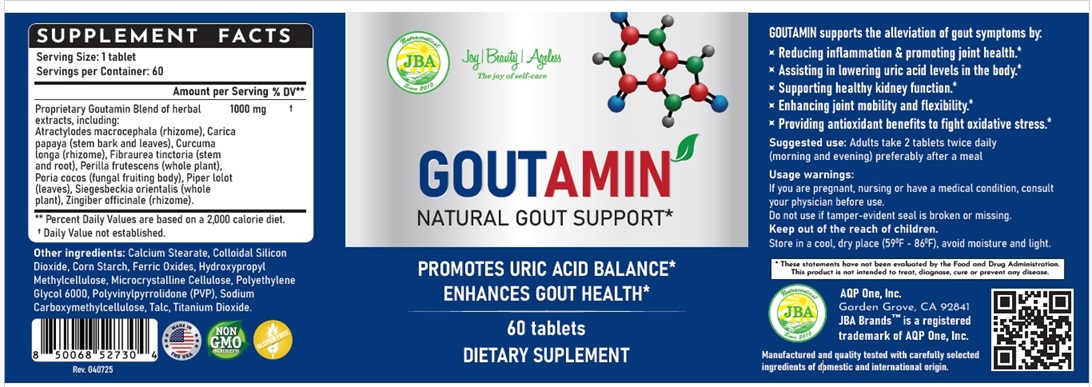 DRUG LABEL: JBA Goutamin
NDC: 13411-873 | Form: TABLET
Manufacturer: Advanced Pharmaceutical Services, Inc. Dba Affordable Quality Pharmaceuticals
Category: otc | Type: HUMAN OTC DRUG LABEL
Date: 20250411

ACTIVE INGREDIENTS: ATRACTYLODES MACROCEPHALA ROOT 116 mg/1 1; CARICA PAPAYA WHOLE 116 mg/1 1; TURMERIC 94 mg/1 1; FIBRAUREA TINCTORIA WHOLE 116 mg/1 1; PERILLA FRUTESCENS WHOLE 116 mg/1 1; WOLFIPORIA COCOS WHOLE 116 mg/1 1; PIPER SARMENTOSUM WHOLE 116 mg/1 1; ZINGIBER OFFICINALE WHOLE 70 mg/1 1; SIGESBECKIA ORIENTALIS WHOLE 140 mg/1 1
INACTIVE INGREDIENTS: CALCIUM STEARATE; SILICON DIOXIDE; STARCH, CORN; FERRIC OXIDE RED; HYPROMELLOSE, UNSPECIFIED; MICROCRYSTALLINE CELLULOSE; POLYETHYLENE GLYCOL 6000; POVIDONE K30; CARBOXYMETHYLCELLULOSE SODIUM, UNSPECIFIED; TALC; TITANIUM DIOXIDE

Identity

Dietary Supplement

Direction

Adults – Take 2 tablets twice daily (morning and evening) preferably after a meal.

Safe handling warning

GOUTAMIN
NATURAL GOUT SUPPORT*
Promotes Uric Acid Balance*
Enhances Gout Health*
GOUTAMIN supports the alleviation of gout symptoms by:
- Reducing inflammation & promoting joint health*
- Assisting in lowering uric acid levels in the body*
- Supporting healthy kidney function*
- Enhancing joint mobility and flexibility*
- Providing antioxidant benefits to fight oxidative stress*

* These statements have not been evaluated by the Food & Drug Administration. This product is not intended to diagnose, treat, cure, or prevent any disease.

WARNINGS

- If you are pregnant, nursing or have a medical condition, consult your physician before use.
- Do not use if tamper-evident seal is broken or missing.
- Keep Out of The Reach of Children.
- Store in a cool, dry place (59oF-86oF), avoid moisture and light.

Other ingredients

Calcium Stearate, Colloidal Silicon Dioxide, Corn Starch, Ferric Oxides, Hydroxypropyl Methylcellulose, Microcrystalline Cellulose, Polyethylene
Glycol 6000, Polyvinylpyrrolidone (PVP), Sodium Carboxymethylcellulose, Talc, Titanium Dioxide.